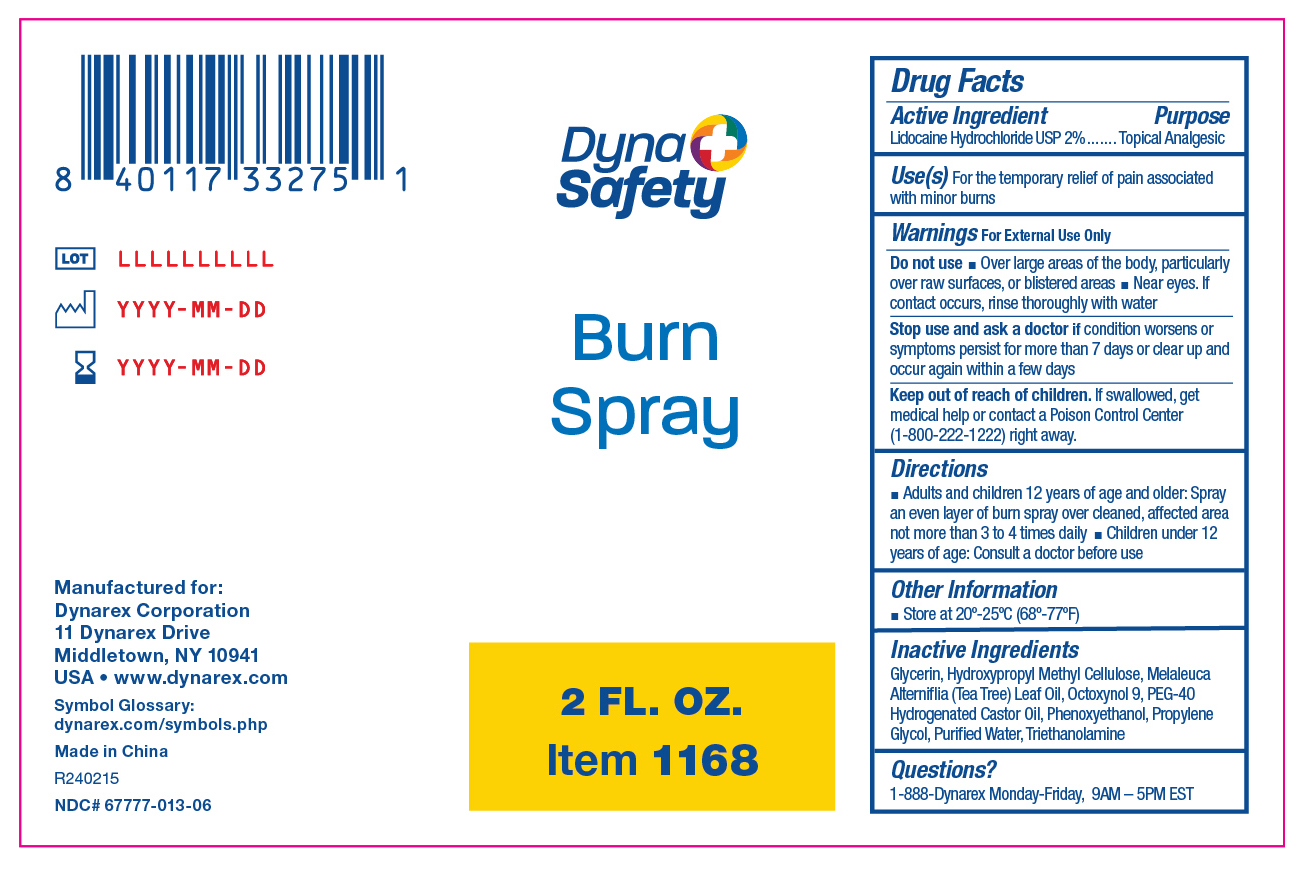 DRUG LABEL: 1168
NDC: 67777-013 | Form: SPRAY
Manufacturer: Dynarex Corporation
Category: otc | Type: HUMAN OTC DRUG LABEL
Date: 20240216

ACTIVE INGREDIENTS: LIDOCAINE HYDROCHLORIDE 0.02 mg/1 mL
INACTIVE INGREDIENTS: MELALEUCA ALTERNIFOLIA (TEA TREE) LEAF OIL; WATER; OCTOXYNOL 9; POLYOXYL 40 HYDROGENATED CASTOR OIL; GLYCERIN; PHENOXYETHANOL; TROLAMINE; HYPROMELLOSE, UNSPECIFIED; PROPYLENE GLYCOL

1168 Burn Spray

Active Ingredient

Lidocaine Hydrochloride 2%

Purpose

Topical Analgesic

Use(s)

For the temporary relief of pain associated with minor burns

Warnings

For External Use Only

Do not use

• Over large areas of the body, particularly over raw surfaces, or blistered areas

• Near eyes. If contact occurs, rinse thoroughly with water.

Stop use and ask a doctor if

Condition worsens or symptoms persist for more than 7 days or clear up and occur again within a few days

Keep out of reach of children

If swallowed, get medical help or contact a Poison Control Center (1-800-222-1222) right away.

Directions

• Adults and children 12 years of age and older: Spray an even layer of burn spray over cleaned, affected area not more than 3 to 4 times daily.

• Children under 12 years of age: Consult a doctor before use

Other Information

• Store at 20º-25ºC (68º-77°F)

Inactive Ingredients

Glycerin, Hydroxypropyl Methyl Cellulose, Melaleuca Alterniflia (Tea Tree) Leaf Oil, Octoxynol 9, PEG-40 Hydrogenated Castor Oil, Phenoxyethanol, Propylene Glycol, Purified Water, Triethanolamine

Questions?

1-888-Dynarex Monday - Friday, 9AM - 5PM EST

Label

1168 Label